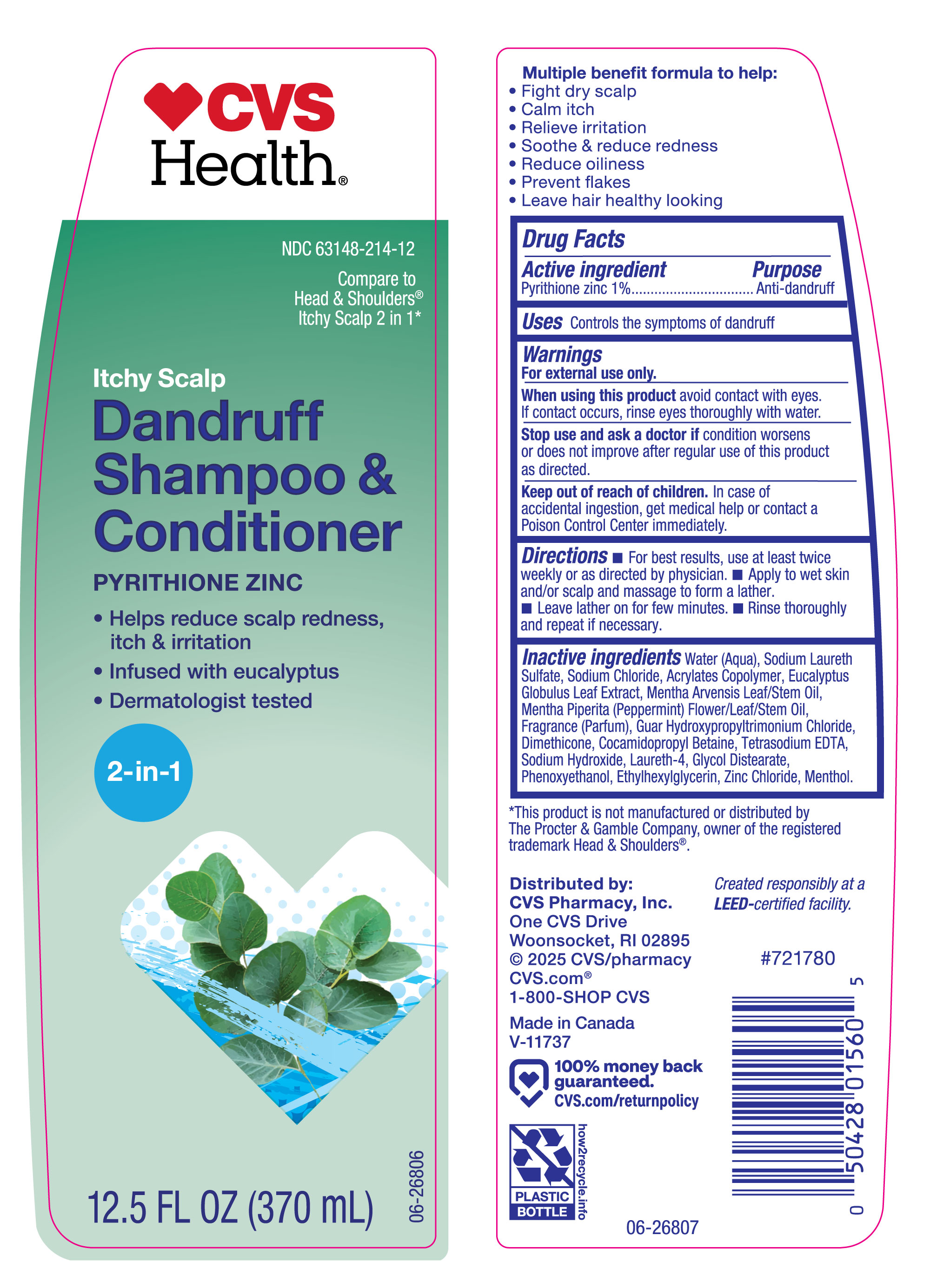 DRUG LABEL: CVS Itchy Scalp
NDC: 63148-214 | Form: SHAMPOO
Manufacturer: Apollo Health and Beauty Care
Category: otc | Type: HUMAN OTC DRUG LABEL
Date: 20251013

ACTIVE INGREDIENTS: PYRITHIONE ZINC 10 mg/1 mL
INACTIVE INGREDIENTS: ACRYLATES/VINYL ISODECANOATE CROSSPOLYMER (10000 MPA.S NEUTRALIZED AT 0.5%); GLYCOL DISTEARATE; PHENOXYETHANOL; SODIUM CHLORIDE; EUCALYPTUS GLOBULUS LEAF; FRAGRANCE CLEAN ORC0600327; SODIUM LAURETH SULFATE; MENTHOL; GUAR HYDROXYPROPYLTRIMONIUM CHLORIDE; LAURETH-4; MENTHA PIPERITA (PEPPERMINT) LEAF; ZINC CHLORIDE; WATER; ETHYLHEXYLGLYCERIN; DIMETHICONE; COCAMIDOPROPYL BETAINE; TETRASODIUM EDTA; SODIUM HYDROXIDE; MENTHA ARVENSIS LEAF OIL

CVS 63148-214, 1% Pyrithione zinc.

Active Ingredient

Pyrithione zinc 1%

Purpose

Anti-dandruff

Uses

Controls the symptoms of dandruff.

Warnings

For external use only.

When using this product

avoid contact with eyes. If contact occurs, rinse eyes throughly with water.

Stop use and ask a doctor if

condition worsens or does not improve after regular use of this product as directed.

Keep out of reach of children.

In case of accidental ingestion, get medical help or contact a Poson Control Center immediately.

Directions

- For best results, use at least twice weekly or as directed by physician.
- Apply to wet skin and/or scalp and massage to form a lather.
- Leave lather on for few minutes.
- Rinse thoroughly and repeat if necessary.

Inactive Ingredients

Water (Aqua), Sodium Laureth Sulfate, Sodium Chloride, Acrylates Copolymer, Eucalyptus Globulus Leaf Extract, Mentha Arvensis Leaf/Stem oil, Mentha Piperita (Peppermint) Flower/Leaf/Stem Oil, Fragrance (Parfum), Guar Hydroxypropyltrimonium Chloride, Dimethicone, Cocamidopropyl Betaine, Tetrasodium EDTA, Sodium Hydroxide, Laureth-4, Glycol Distearate, Phenoxyethanol, Ethylhexylglycerin, Zinc Chloride, Menthol.